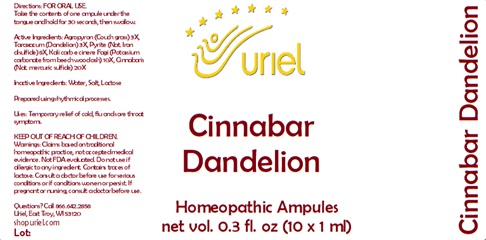 DRUG LABEL: Cinnabar Dandelion
NDC: 48951-4195 | Form: LIQUID
Manufacturer: Uriel Pharmacy Inc.
Category: homeopathic | Type: HUMAN OTC DRUG LABEL
Date: 20241219

ACTIVE INGREDIENTS: ELYMUS REPENS ROOT 3 [hp_X]/1 mL; TARAXACUM PALUSTRE ROOT 3 [hp_X]/1 mL; FERROUS CATION 8 [hp_X]/1 mL; CARBONATE ION 10 [hp_X]/1 mL; MERCURIC CATION 20 [hp_X]/1 mL
INACTIVE INGREDIENTS: WATER; SODIUM CHLORIDE; LACTOSE

Cinnabar Dandelion

INDICATIONS AND USAGE

Directions: FOR ORAL USE.

DOSAGE AND ADMINISTRATION

Take the contents of one ampule under the tongue and hold for 30 seconds, then swallow.

ACTIVE INGREDIENT

Active Ingredients: Agropyron (Couch grass) 3X, Taraxacum (Dandelion) 3X, Pyrite (Nat. Iron disulfide) 8X, Kali carb e cinere Fagi (Potassium carbonate from beech wood ash) 10X, Cinnabaris (Nat. mercuric sulfide) 20X

Inactive Ingredients: Water, Salt, Lactose

Prepared using rhythmical processes.

PURPOSE

Uses: Temporary relief of cold, flu and sore throat symptoms.

KEEP OUT OF REACH OF CHILDREN.

WARNINGS

Warnings: Claims based on traditional homeopathic practice, not accepted medical evidence. Not FDA evaluated. Do not use if allergic to any ingredient. Contains traces of lactose. Consult a doctor before use for serious conditions or if conditions worsen or persist. If pregnant or nursing, consult a doctor before use.

QUESTIONS

Questions? Call 866.642.2858 Uriel, East Troy, WI 53120 shopuriel.com Lot: